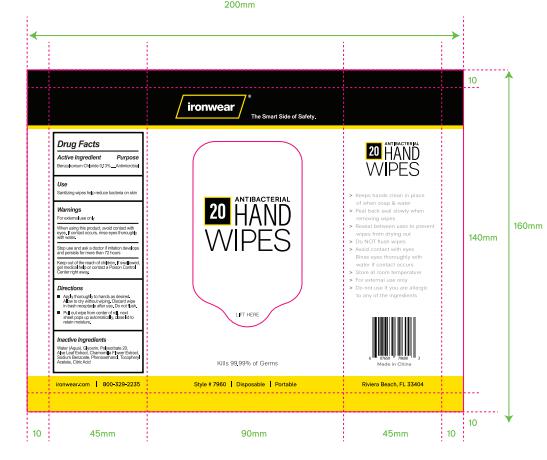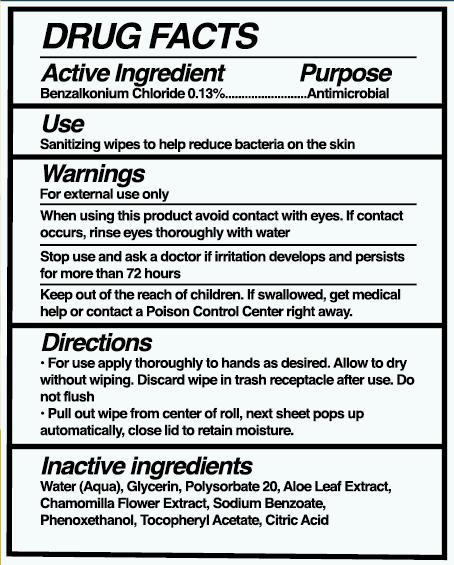 DRUG LABEL: Sanitizing Hand Wipes
NDC: 78936-023 | Form: CLOTH
Manufacturer: Hangzhou Caring Cleaning Commodity Co.,Ltd
Category: otc | Type: HUMAN OTC DRUG LABEL
Date: 20210122

ACTIVE INGREDIENTS: BENZALKONIUM CHLORIDE 1.3 mg/1 1
INACTIVE INGREDIENTS: ALOE VERA LEAF; ALPHA-TOCOPHEROL ACETATE; WATER; GLYCERIN; SODIUM BENZOATE; PHENOXYETHANOL; POLYSORBATE 20; CHAMOMILE; CITRIC ACID ACETATE

Sanitizing Hand Wipes

Active Ingredient(s)

Benzalkonium Chloride 0.13%

Purpose

Antimicrobial

Use

Sanitizing wipes to help reduce bacteria on skin

Warnings

For external use only.

When using this product

Avoid contact with eyes. If contact occurs, rinse eyes thoroughly with water

Stop use and ask a doctor if irritation develops and persists for more than 72 hours.

Keep out of reach of children

Keep out of the reach of children. If swallowed, get medical help or contact a Poison Control Center right away.

Directions

- For use apply thoroughly to hands as desired. Allow to dry without wiping. Discard wipe in trash receptacle after use. Do not flush.
- Pull put wipe from center of roll, next sheet pops up automatically, close lid to retain moisture.

Inactive ingredients

Water (Aqua), Glycerin, Polysorbate 20, Aloe Leaf Extract, Chamomilla Flower Extract, Sodium Benzoate, Phenoxethanol, Tocopheryl Acetate, Citric Acid

Package Label - Principal Display Panel

20 CLOTH IN 1 PACKAGE NDC: 78936-023-01

160 CLOTH IN 1 CANISTER NDC: 78936-023-02